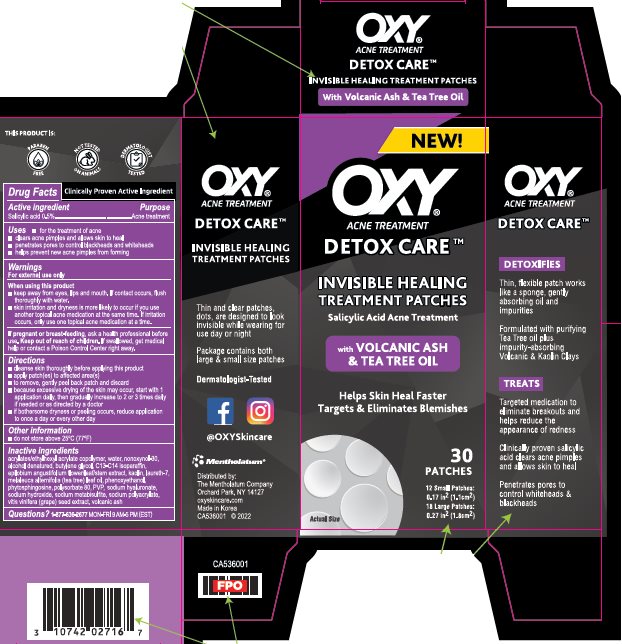 DRUG LABEL: Oxy
NDC: 10742-1101 | Form: PATCH
Manufacturer: The Mentholatum Company
Category: otc | Type: HUMAN OTC DRUG LABEL
Date: 20241213

ACTIVE INGREDIENTS: SALICYLIC ACID 5 mg/1 1
INACTIVE INGREDIENTS: 2-ETHYLHEXYL ACRYLATE; WATER; NONOXYNOL-30; ALCOHOL; BUTYLENE GLYCOL; C13-14 ISOPARAFFIN; EPILOBIUM ANGUSTIFOLIUM WHOLE; KAOLIN; LAURETH-7; TEA TREE OIL; PHENOXYETHANOL; PHYTOSPHINGOSINE; POLYSORBATE 80; POVIDONE, UNSPECIFIED; HYALURONATE SODIUM; SODIUM HYDROXIDE; SODIUM METABISULFITE; SODIUM POLYACRYLATE (8000 MW); VITIS VINIFERA SEED

Drug Facts - Oxy Detox Care Invisible Healing Treatment Patches

Active ingredient

Salicylic acid 0.5%

Purpose

Salicylic acid - Acne treatment

Uses

- for the treatment of acne
- clears acne pimples and allows skin to heal
- penetrates pores to control blackheads and whiteheads
- helps prevent new acne pimples from forming

Warnings

For external use only

When using this product

- keep away from eyes, lips and mouth. If contact occurs, flush thoroughly with water.
- skin irritation and dryness is more likely to occur if you use another topical acne medication at the same time. If irritation occurs, only use one topical acne medication at a time.

If pregnant or breast-feeding

ask a health professional before use.

Keep out of reach of children.

If swallowed, get medical help or contact a Poison Control Center right away.

Directions

- cleanse skin thoroughly before applying this product
- apply patch(es) to affected area(s)
- to remove, gently peel back patch and discard
- because excessive drying of the skin may occur, start with 1 application daily, then gradually increase to 2 or 3 times daily if needed or as directed by a doctor
- if bothersome dryness or peeling occurs, reduce application to once a day or every other day

Storage and Handling

- do not store above 25OC (77OF)

Inactive ingredients

acrylates/ethylhexyl acrylate copolymer, water, nonoxynol-30, alcohol denatured, butylene glycol, C13-14 isoparaffin, epilobium angustifolium flower/leaf/stem extract, kaolin, laureth-7, melaleuca alternifolia (tea tree) leaf oil, phenoxyethanol, phytosphingosine, polysorbate 80, PVP, sodium hyaluronate, sodium hydroxide, sodium metabisulfite, sodium polyacrylate, vitis vinifera (grape) seed extract, volcanic ash

Questions?

1-877-636-2677 MON-FRI 9 AM - 5 PM (EST)